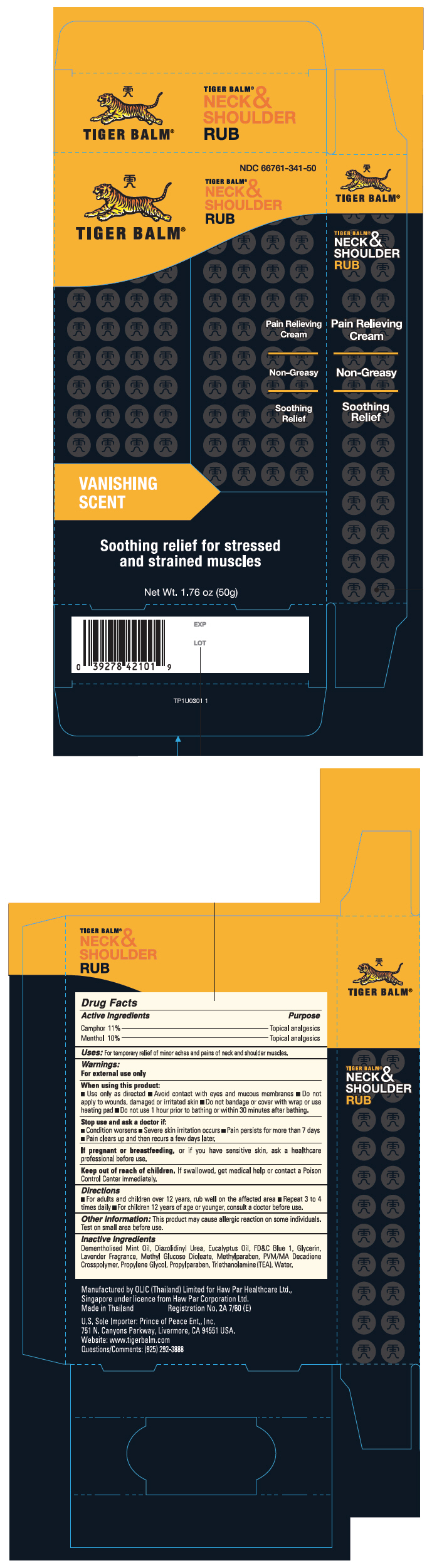 DRUG LABEL: Tiger Balm 

NDC: 66761-341 | Form: CREAM
Manufacturer: Haw Par Healthcare Ltd.
Category: otc | Type: HUMAN OTC DRUG LABEL
Date: 20260209

ACTIVE INGREDIENTS: CAMPHOR (SYNTHETIC) 11 mg/1 g; MENTHOL, UNSPECIFIED FORM 10 mg/1 g
INACTIVE INGREDIENTS: DIAZOLIDINYL UREA; EUCALYPTUS OIL; FD&C BLUE NO. 1; GLYCERIN; PEG-120 METHYL GLUCOSE DIOLEATE; METHYLPARABEN; PROPYLENE GLYCOL; PROPYLPARABEN; TROLAMINE; WATER

TIGER BALM®
NECK &
SHOULDER
RUB

Drug Facts

Active Ingredients

Camphor 11%, Menthol 10%

Purpose

Topical analgesics

Uses

For temporary relief of minor aches and pains of neck and shoulder muscles and joints

Warnings

For external use only

When using this product:

- Use only as directed
- Avoid contact with eyes and mucous membranes
- Do not apply to wounds, damaged or irritated skin
- Do not bandage or cover with wrap or use heating pad
- Do not use 1 hour prior to bathing or 30 minutes after bathing.

Stop use and ask a doctor if:

- Condition worsens
- Severe skin irritation occurs
- Pain persists for more than 7 days
- Pain clears up and then recurs a few days later.

PREGNANCY OR BREAST FEEDING

If pregnant or breastfeeding,or if you have sensitive skin, ask a healthcare professional before use.

Keep out of reach of children.If swallowed, get medical help or contact a Poison Control Center immediately.

Directions

- For adults and children over 12 years, rub well on the affected area
- Repeat 3 to 4 times daily
- For children 12 years of age or younger, consult a doctor before use.

Other information

This product may cause allergic reaction in some individuals. Test on small area before use.

Inactive Ingredients

Dementholised Mint Oil, Diazolidinyl Urea, Eucalyptus Oil, FD&C Blue 1, Glycerin, Lavender Fragrance, Methyl Glucose Dioleate, Methylparaben, PVM/MA Decadiene Crosspolymer, Propylene Glycol, Propylparaben, Triethanolamine (TEA), Water.

Manufactured for Haw Par Healthcare Ltd., Singapore under licence from Haw Par Corporation Ltd.

Questions/Comments

(510) 887-1899

PRINCIPAL DISPLAY PANEL - 50g Tube Carton

NDC 66761-341-50

TIGER BALM®

TIGER BALM®
NECK &
SHOULDER
RUB

Pain Relieving
Cream

Non-Greasy

Soothing
Relief

VANISHING
SCENT

Soothing relief for stressed
and strained muscles

Net Wt. 1.76 oz (50g)